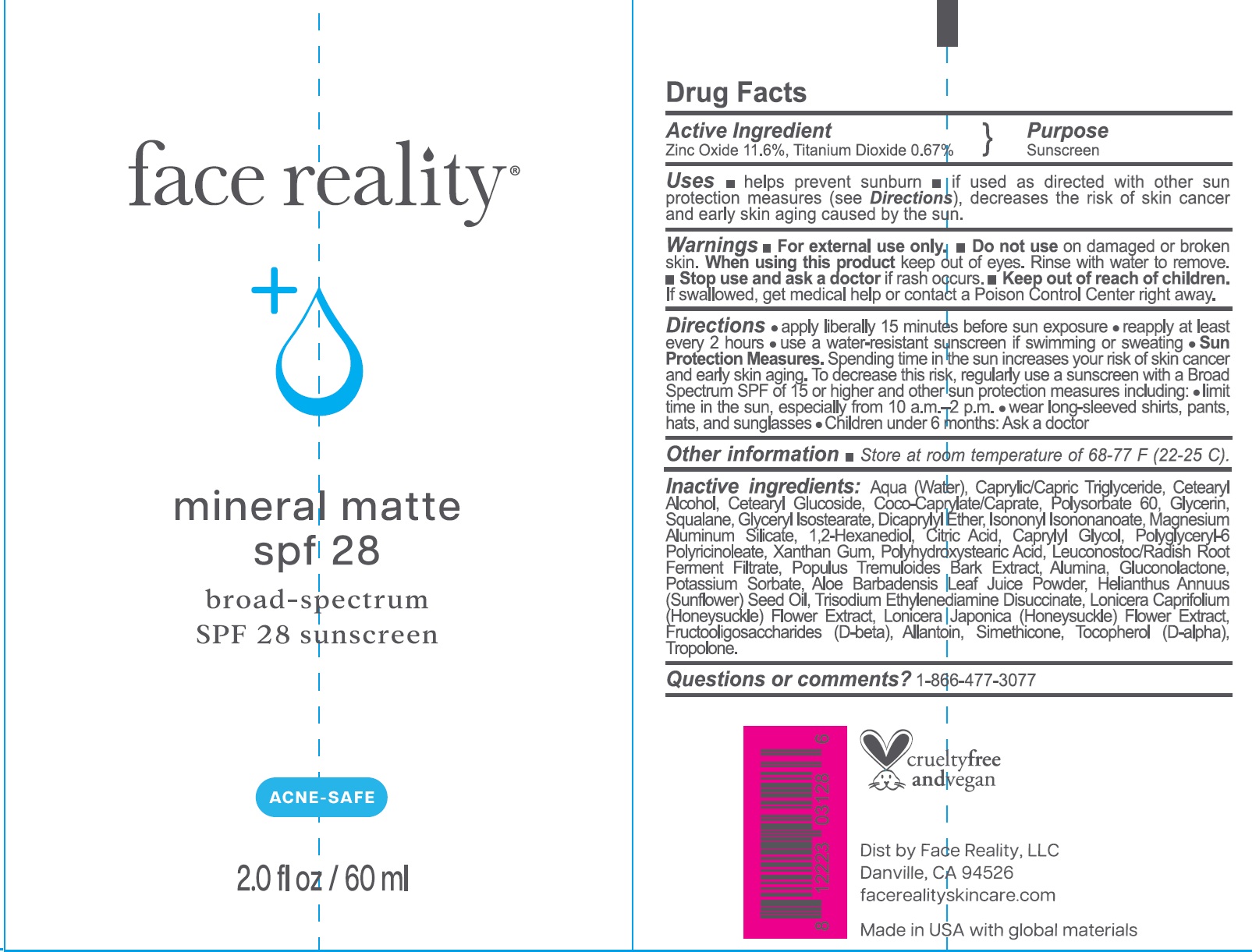 DRUG LABEL: Face Reality mineral matte spf 28 Sunscreen SPF 28
NDC: 70707-454 | Form: CREAM
Manufacturer: Face Reality, LLC
Category: otc | Type: HUMAN OTC DRUG LABEL
Date: 20241220

ACTIVE INGREDIENTS: ZINC OXIDE 116 mg/1 mL; TITANIUM DIOXIDE 6.7 mg/1 mL
INACTIVE INGREDIENTS: WATER; MEDIUM-CHAIN TRIGLYCERIDES; CETOSTEARYL ALCOHOL; CETEARYL GLUCOSIDE; COCOYL CAPRYLOCAPRATE; POLYSORBATE 60; GLYCERIN; SQUALANE; GLYCERYL ISOSTEARATE; DICAPRYLYL ETHER; ISONONYL ISONONANOATE; MAGNESIUM ALUMINUM SILICATE; 1,2-HEXANEDIOL; CITRIC ACID MONOHYDRATE; CAPRYLYL GLYCOL; POLYGLYCERYL-6 POLYRICINOLEATE; XANTHAN GUM; LEUCONOSTOC/RADISH ROOT FERMENT FILTRATE; POPULUS TREMULOIDES BARK; ALUMINA; GLUCONOLACTONE; POTASSIUM SORBATE; ALOE BARBADENSIS LEAF JUICE POWDER; SUNFLOWER OIL; TRISODIUM ETHYLENEDIAMINE DISUCCINATE; LONICERA CAPRIFOLIUM FLOWER; LONICERA JAPONICA FLOWER; ALLANTOIN; TOCOPHEROL; TROPOLONE

Face Reality mineral matte spf 28 Sunscreen SPF 28

Active Ingredient

Zinc Oxide 11.6%, Titanium Dioxide 0.67%

Purpose

Sunscreen

Uses

- helps prevent sunburn
- if used as directed with other sun protection measures (see Directions), decreases the risk of skin cancer and early skin aging caused by the sun.

Warnings

- For external use only.

Do not use

- on damaged or broken skin.

When using this product

keep out of eyes. Rinse with water to remove.

Stop use and ask a doctor

- if rash occurs.

Keep out of reach of children.

- If swallowed, get medical help or contact a Poison Control Center right away.

Directions

- apply liberally 15 minutes before sun exposure
- reapply at least every 2 hours
- use a water-resistant sunscreen if swimming or sweating
- Sun Protection Measures.Spending time in the sun increases your risk of skin cancer and early skin aging. To decrease this risk, regularly use a sunscreen with a Broad Spectrum SPF of 15 or higher and other sun protection measures including:
- limit time in the sun, especially from 10 a.m.-2 p.m.
- wear long-sleeved shirts, pants, hats, and sunglasses
- Children under 6 months: Ask a doctor

Other information

- Store at room temperature of 68-77 F (22-25 C).

Inactive ingredients:

Aqua (Water), Caprylic/Capric Triglyceride, Cetearyl Alcohol, Cetearyl Glucoside, Coco-Caprylate/Caprate, Polysorbate 60, Glycerin, Squalane, Glyceryl Isostearate, Dicaprylyl Ether, Isononyl Isononanoate, Magnesium Aluminum Silicate, 1,2-Hexanediol, Citric Acid, Caprylyl Glycol, Polyglyceryl-6 Polyricinoleate, Xanthan Gum, Polyhydroxystearic Acid, Leuconostoc/Radish Root Ferment Filtrate, Populus Tremuloides Bark Extract, Alumina, Gluconolactone, Potassium Sorbate, Aloe Barbadensis Leaf Juice Powder, Helianthus Annuus (Sunflower) Seed Oil, Trisodium Ethylenediamine Disuccinate, Lonicera Caprifolium (Honeysuckle) Flower Extract, Lonicera Japonica (Honeysuckle) Flower Extract, Fructooligosaccharides (D-beta), Allantoin, Simethicone, Tocopherol (D-alpha), Tropolone.

Questions or comments?

1-866-477-3077